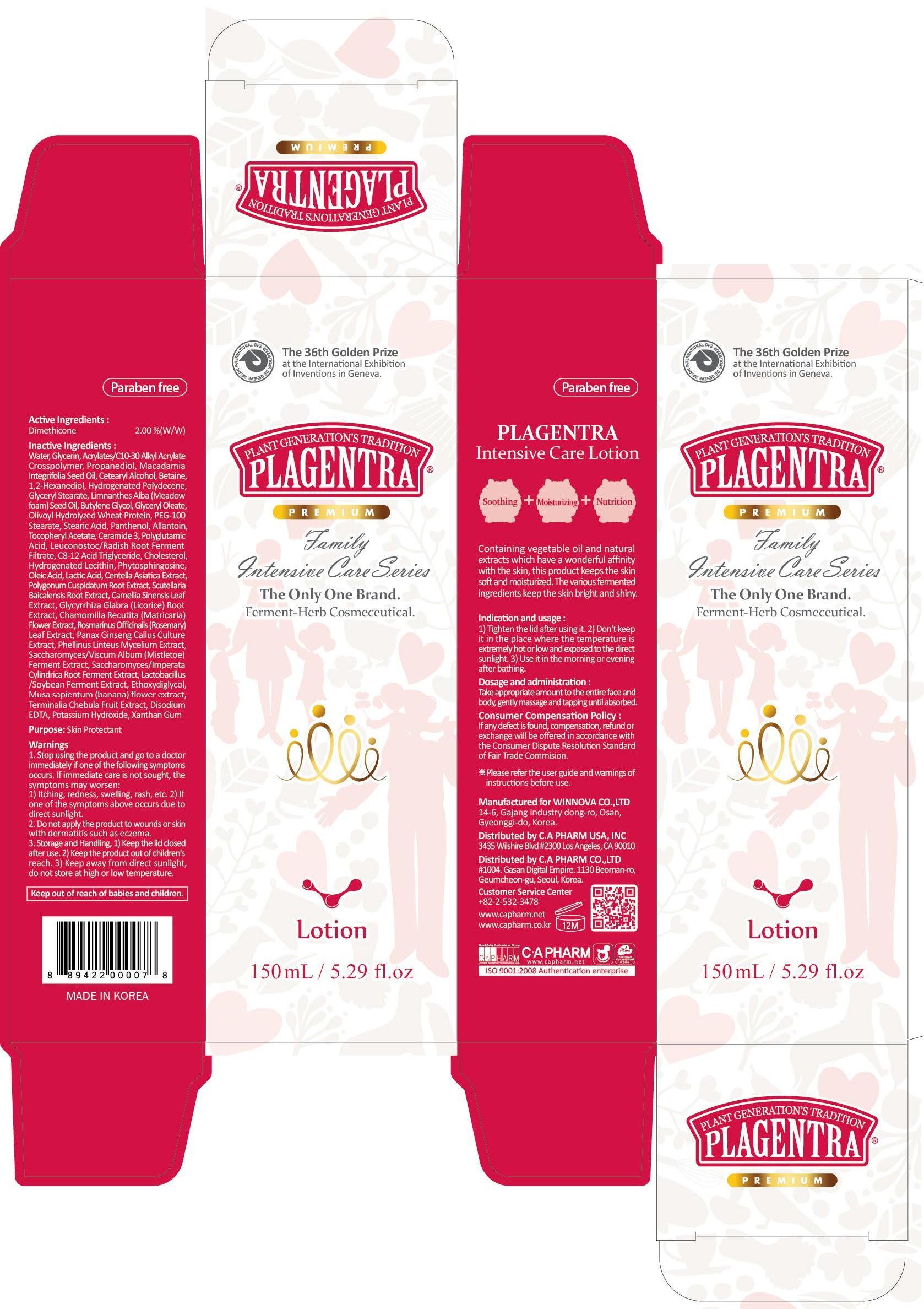 DRUG LABEL: PLAGENTRA INTENSIVE CARE
NDC: 68988-050 | Form: LOTION
Manufacturer: C.A Pharm Co., Ltd.
Category: otc | Type: HUMAN OTC DRUG LABEL
Date: 20141205

ACTIVE INGREDIENTS: Dimethicone 3 mg/150 mL
INACTIVE INGREDIENTS: Water; Glycerin

ACTIVE INGREDIENT

Active Ingredient: Dimethicone 2%

INACTIVE INGREDIENT

Inactive Ingredients:
Water, Glycerin, Acrylates/C10-30 Alkyl Acrylate Crosspolymer, Propanediol, Macadamia Integrifolia Seed Oil, Cetearyl Alcohol, Betaine, 1,2-Hexanediol, Hydrogenated Polydecene, Glyceryl Stearate, Limnanthes Alba (Meadowfoam) Seed Oil, Butylene Glycol, Glyceryl Oleate, Olivoyl Hydrolyzed Wheat Protein, PEG-100 Stearate, Stearic Acid, Panthenol, Allantoin, Tocopheryl Acetate, Ceramide 3, Polyglutamic Acid, Leuconostoc/Radish Root Ferment Filtrate, C8-12 Acid Triglyceride, Cholesterol, Hydrogenated Lecithin, Phytosphingosine, Oleic Acid, Lactic Acid, Centella Asiatica Extract, Polygonum Cuspidatum Root Extract, Scutellaria Baicalensis Root Extract, Camellia Sinensis Leaf Extract, Glycyrrhiza Glabra (Licorice) Root Extract, Chamomilla Recutita (Matricaria) Flower Extract, Rosmarinus Officinalis (Rosemary) Leaf Extract, Panax Ginseng Callus Culture Extract, Phellinus Linteus Mycelium Extract, Saccharomyces/Viscum Album (Mistletoe) Ferment Extract, Saccharomyces/Imperata Cylindrica Root Ferment Extract, Lactobacillus/Soybean Ferment Extract, Ethoxydiglycol, Musa sapientum (banana) flower extract, Terminalia Chebula Fruit Extract, Disodium EDTA, Potassium Hydroxide, Xanthan Gum

PURPOSE

Purpose: Skin Portectant

WARNINGS

1. Stop using the product and go to a doctor immediately if one of the following symptoms occurs. If immediate care is not sought, the symptoms may worsen :
1) Itching, redness, swelling, rash, etc. 2) If one of the symptoms above occurs due to direct sunlight.
2. Do not apply the product to wounds or skin with dermatitis such as eczema.
3. Storage and Handling, 1) Keep the lid closed after use. 2) Keep the product out of children's reach. 3) Keep away from direct sunlight, do not store at high or low temperature.
4. It contains AHA. If it is your first time to use this product, take a small amount and gently apply to the skin to check if it cause andy trouble to your skin.

KEEP OUT OF REACH OF CHILDREN

Keep out of reach of babies and children.

INDICATIONS & USAGE

Indication and usage:
1) Tighten the lid after using it. 2) Don't keep it in the place where the temperature is extremely hot or low and exposed to the direct sunlight. 3) Use it in the morning or evening after shower.

DOSAGE & ADMINISTRATION

Dosage and administration:
Take appropriate amount to the entire face and body, gently massage and tapping until absorbed.